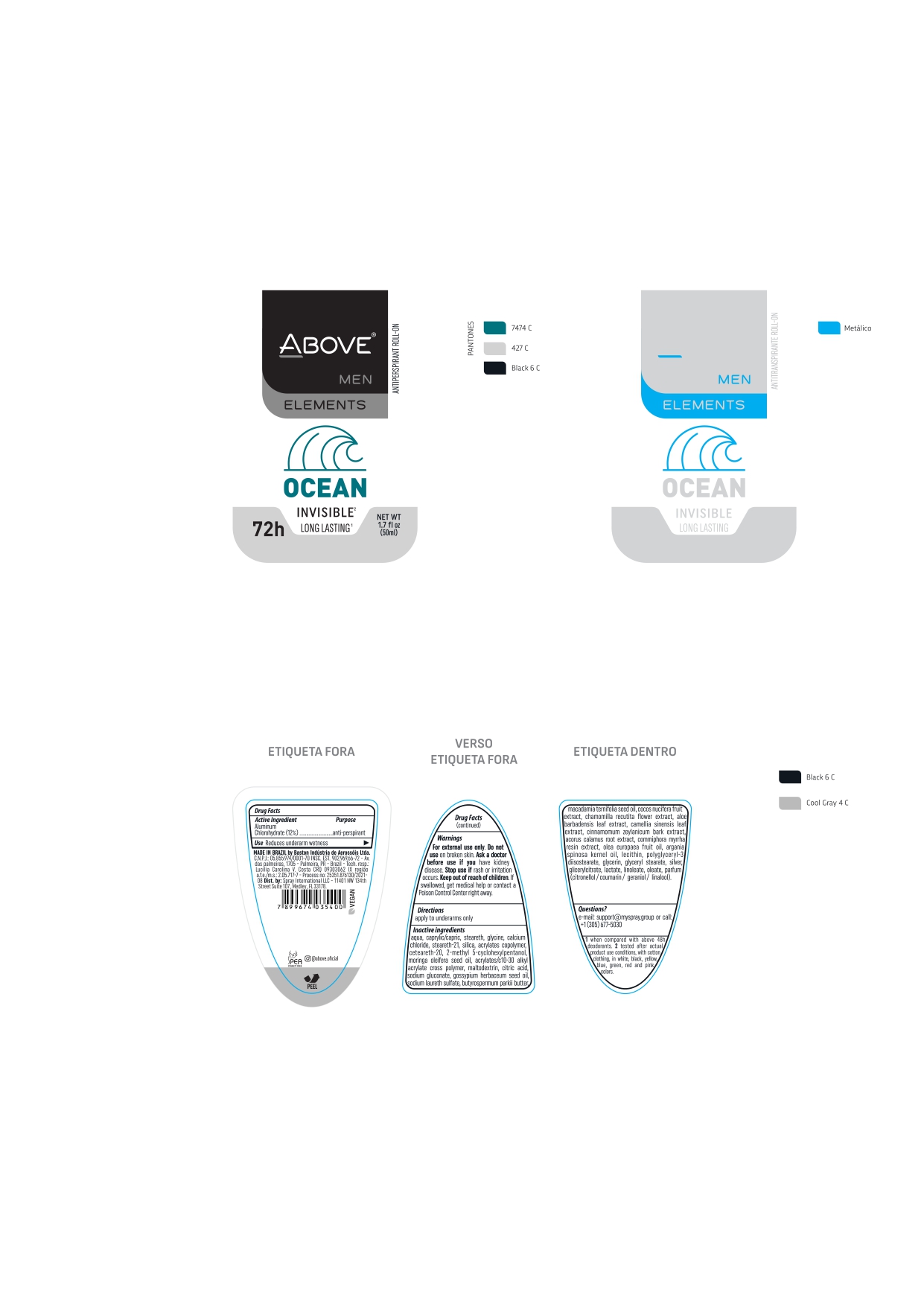 DRUG LABEL: ABOVE MEN ELEMENTS OCEAN INVISIBLE
NDC: 73306-1132 | Form: CREAM
Manufacturer: BASTON INDUSTRIA DE AEROSSOIS LTDA
Category: otc | Type: HUMAN OTC DRUG LABEL
Date: 20241226

ACTIVE INGREDIENTS: ALUMINUM CHLOROHYDRATE 12 mg/100 g
INACTIVE INGREDIENTS: MEDIUM-CHAIN TRIGLYCERIDES

ABOVE MEN ELEMENTS OCEAN INVISIBLE